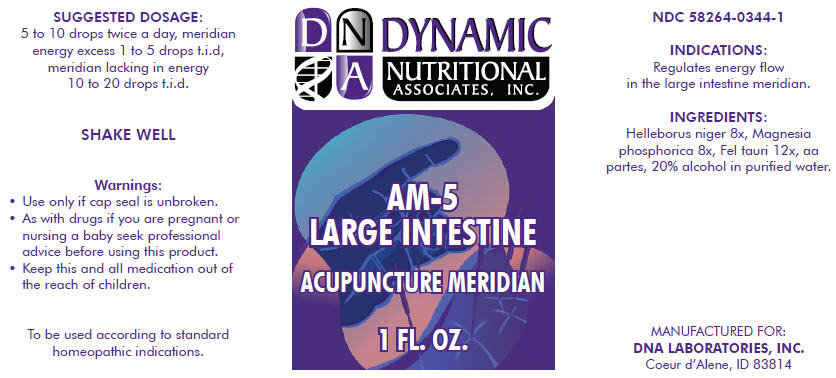 DRUG LABEL: AM-5
NDC: 58264-0344 | Form: SOLUTION
Manufacturer: DNA Labs, Inc.
Category: homeopathic | Type: HUMAN OTC DRUG LABEL
Date: 20250109

ACTIVE INGREDIENTS: HELLEBORUS NIGER WHOLE 8 [hp_X]/1 mL; MAGNESIUM PHOSPHATE, DIBASIC TRIHYDRATE 8 [hp_X]/1 mL; BOS TAURUS BILE 12 [hp_X]/1 mL
INACTIVE INGREDIENTS: ALCOHOL; WATER

AM-5

NDC 58264-0344-1

INDICATIONS

PURPOSE

Regulates energy flow in the large intestine meridian.

INGREDIENTS

INACTIVE INGREDIENT

Helleborus niger 8x, Magnesia phosphorica 8x, Fel tauri 12x, aa partes, 20% alcohol in purified water.

SUGGESTED DOSAGE

5 to 10 drops twice a day, meridian energy excess 1 to 5 drops t.i.d, meridian lacking in energy 10 to 20 drops t.i.d.

STORAGE AND HANDLING

SHAKE WELL

Warnings

- Use only if cap seal is unbroken.

PREGNANCY OR BREAST FEEDING

- As with drugs if you are pregnant or nursing a baby seek professional advice before using this product.

KEEP OUT OF REACH OF CHILDREN

- Keep this and all medication out of the reach of children.

To be used according to standard homeopathic indications.

PRINCIPAL DISPLAY PANEL - 1 FL. OZ. Bottle Label

DYNAMIC
NUTRITIONAL
ASSOCIATES, INC.

AM-5

LARGE INTESTINE

ACUPUNCTURE MERIDIAN

1 FL. OZ.